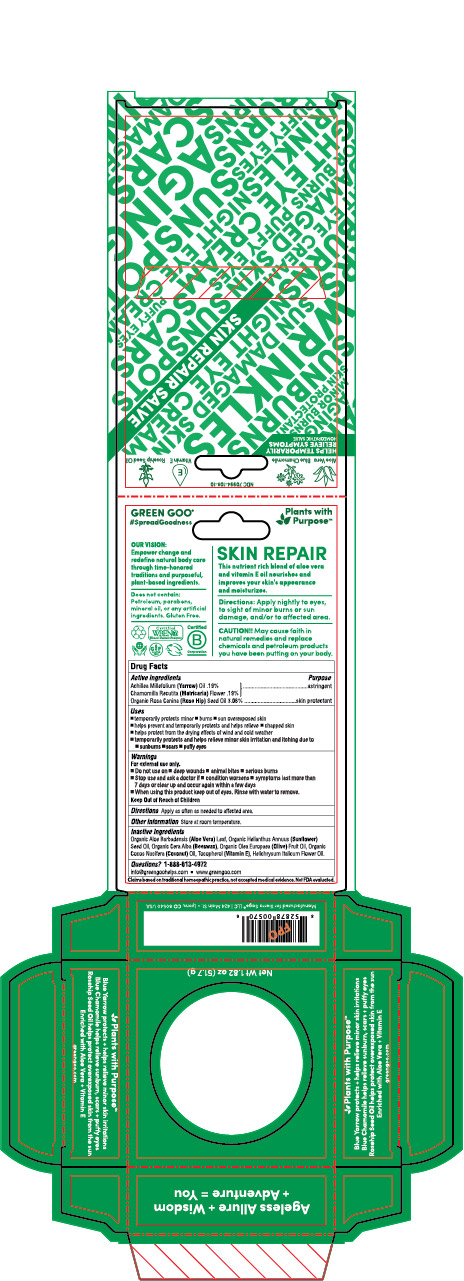 DRUG LABEL: Skin Repair
NDC: 70994-108 | Form: SALVE
Manufacturer: Spry Life LLC
Category: homeopathic | Type: HUMAN OTC DRUG LABEL
Date: 20251215

ACTIVE INGREDIENTS: ROSA MOSCHATA OIL 3.06 g/100 g; MATRICARIA RECUTITA 0.19 g/100 g; ACHILLEA MILLEFOLIUM 0.19 g/100 g
INACTIVE INGREDIENTS: HELICHRYSUM ITALICUM FLOWER OIL; YELLOW WAX; ALPHA-TOCOPHEROL; ALOE VERA LEAF; OLIVE OIL; SUNFLOWER OIL; COCONUT OIL

Skin Repair

Purpose Section

Skin Protectant

Astringent

Active Ingredients

Organic Rosa Canina (Rosehip Seed) Oil 3.06%

Achillea Millefolium (Blue Yarrow) Oil .19%

Chamomilla Recutita (Matricaria) Flower Oil .19%

Indications & Usage

■ temporarily protects minor ■ burns ■ sun overexposed skin
■ helps prevent and temporarily protects and helps relieve ■ chapped skin
■ helps protect from the drying effects of wind and cold weather
■ temporarily protects and helps relieve minor skin irritation and itching due to ■ sunburns ■ scars ■ puffy eyes

Keep out of reach of children section

Keep out of reach of children.

Warnings Section

Warnings

For external use only.

■ Do not use on ■ on deep wounds ■ animal bites ■ serious burns
■ Stop use and ask a doctor if ■ condition worsens ■ symptoms last more than 7 days or clear up and occur again within a few days

■ When using this product keep out of eyes. Rinse with water to remove.

Storage

Store at room temperature.

Dosage & Administration Section

Apply as often as needed to affected area.

Inactive Ingredients

Organic Aloe Barbadensis (Aloe Vera) Leaf, Organic Helianthus Annuus (Sunflower) Seed Oil, Organic Cera Alba (Beeswax), Organic Olea Europaea (Olive) Fruit Oil, Organic Cocos Nucifera (Coconut) Oil, Tocopherol (Vitamin E), Helichrysum Italicum Flower Oil.